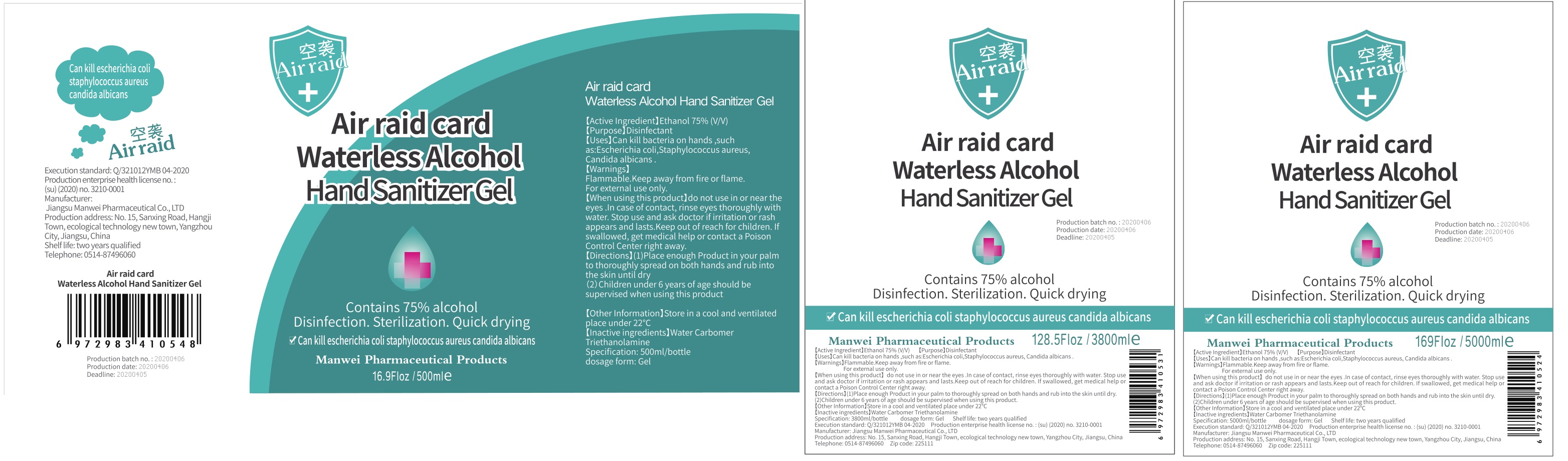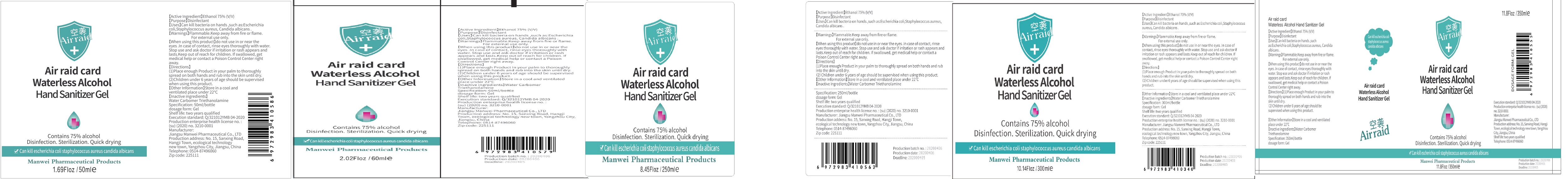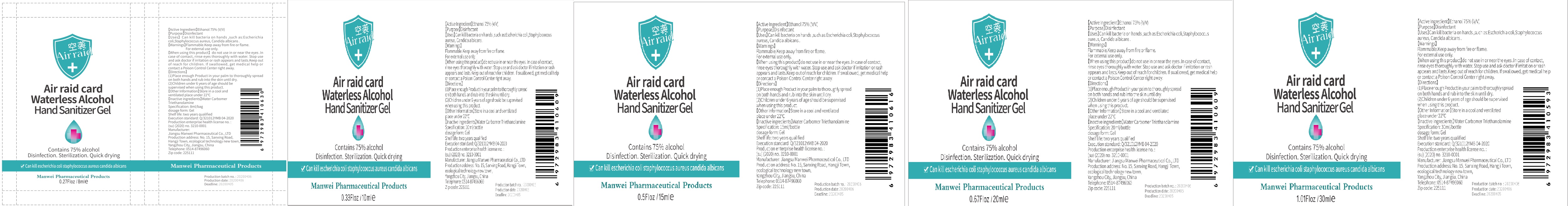 DRUG LABEL: Waterless Alcohol Hand Sanitizer Gel
NDC: 75086-009 | Form: GEL
Manufacturer: Jiangsu Manwei Pharmaceutical Co.,Ltd
Category: otc | Type: HUMAN OTC DRUG LABEL
Date: 20200429

ACTIVE INGREDIENTS: ALCOHOL 75 mL/100 mL
INACTIVE INGREDIENTS: CARBOMER 934; TROLAMINE; WATER

Waterless Alcohol Hand Sanitizer Gel

Active Ingredient

Ethanol 75%(V/V)

Purpose

Disinfectant

Uses

Can kill bacteria on hands suchas: Escherichia coli, Staphylococcus aureusCandida albicans

Warnings

Flammable. Keep away from fire or flame For external use only

When using this product]do not use in or near the eyes. In case of contact, rinse eyes thoroughly with water Stop use and ask doctor if irritation or rash appears and lasts. Keep out of reach for children. If swallowed, get medical help or contact a Poison Control Center right away.

Directions

- Place enough Product in your palm to thoroughly spread on both hands and rub into the skin until dry
- Children under 6 years of age should be supervised when using this product

Other information

Store in a cool and ventilated place under 22 C

Inactive ingredients

Weter Carbomer Triethanolamine